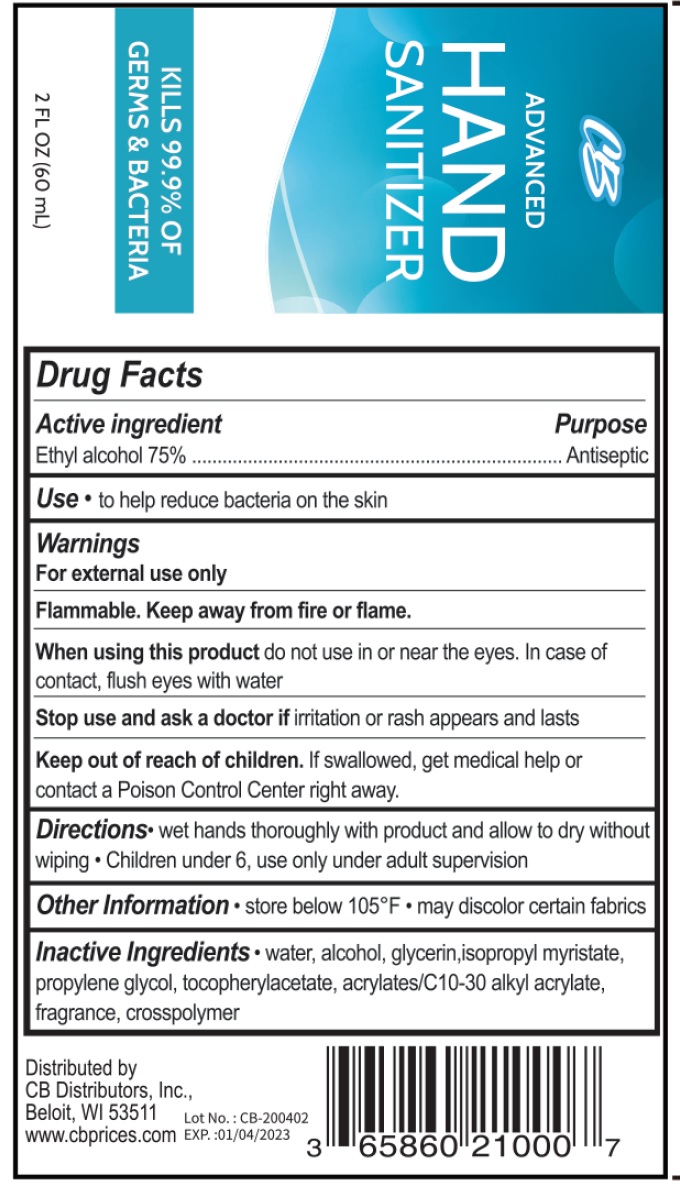 DRUG LABEL: CB Advanced Hand Sanitizer
NDC: 76813-005 | Form: GEL
Manufacturer: Cb Distributors, Inc.
Category: otc | Type: HUMAN OTC DRUG LABEL
Date: 20200430

ACTIVE INGREDIENTS: ALCOHOL 0.75 mL/1 mL
INACTIVE INGREDIENTS: WATER; GLYCERIN; ISOPROPYL MYRISTATE; PROPYLENE GLYCOL; .ALPHA.-TOCOPHEROL ACETATE

CB Advanced Hand Sanitizer

Active ingredient

Ethyl alcohol 75%

Purpose

Antiseptic

Uses

- to help reduce bacteria on the skin

Warnings

For external use only

Flammable, Keep away from fire or flame.

When using this product

- do not use in or near the eyes. In case of contact, flush eyes with water

Stop use and ask a doctor if

- irritation or rash appears and lasts

Keep out of reach of children.

If swallowed, get medical help or contact a Poison Control Center right away.

Directions

- wet hands thoroughly with product and allow to dry without wiping
- Children under 6, use only under adult supervision

Other Information

- store below 105°F
- may discolor certain fabrics

Inactive ingredients

water, alcohol, glycerin, isopropyl myristate, propylene glycol, tocopherylacetate, acrylate/c10-30 alkyl acrylate, fragrance, crosspolymer,